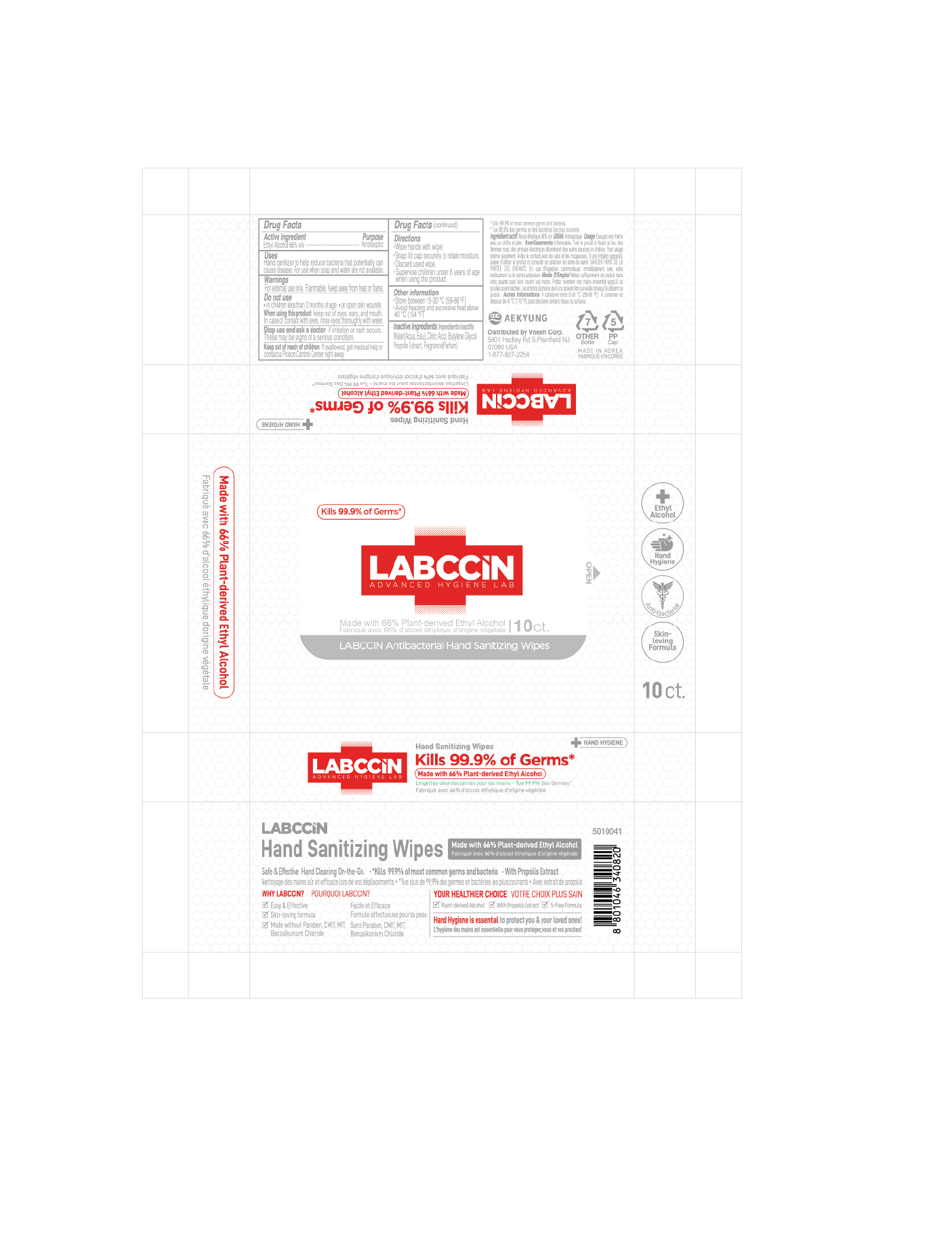 DRUG LABEL: LABCCIN Antibacterial hand Sanitizing Wipes
NDC: 67225-1066 | Form: CLOTH
Manufacturer: Aekyung Industrial Co., Ltd.
Category: otc | Type: HUMAN OTC DRUG LABEL
Date: 20200518

ACTIVE INGREDIENTS: ALCOHOL 0.66 1/1 1
INACTIVE INGREDIENTS: PROPOLIS WAX; ANHYDROUS CITRIC ACID; BUTYLENE GLYCOL; WATER

LABCCIN Antibacterial hand Sanitizing Wipes 67225-1066-1

Active Ingredient(s)

Ethyl Alcohol 66% v/v Purpose: Antiseptic

Purpose

Antiseptic, Hand Sanitizer Wipes

Use

Hand sanitizer to reduce bacteria that potentially can cause disease. For use when soap and water are not available.

Warnings

For external use only

Flammable. Keep away from heat and flame.

When using this product

keep out of eyes, ears, and mouth. In case of contact with eyes, rinse eyes thoroughly with water.

Keep out of reach of children. If swallowed, get medical help or contact a Poison Control Center right away.

Directions

- Wipe hands thoroughly for approximately 30 seconds
- discard after single use
- Supervise children under 6 years of age when using this product to avoid swallowing

Other information

store between 15-40°C (59-105ºF) avoid freezing and excessive heat above 40°C (104ºF)

Inactive ingredients

water (aqua), citric acid, butylene glycol, propolis extract, fragrance (parfum)